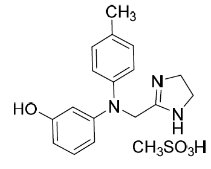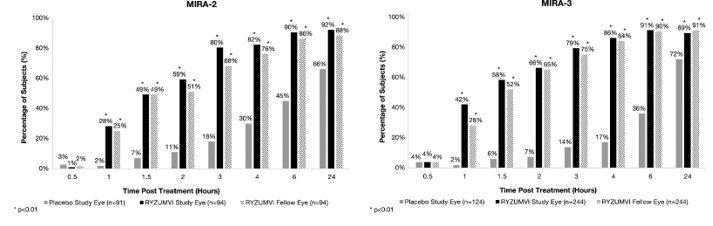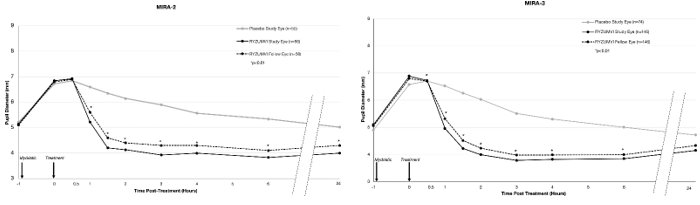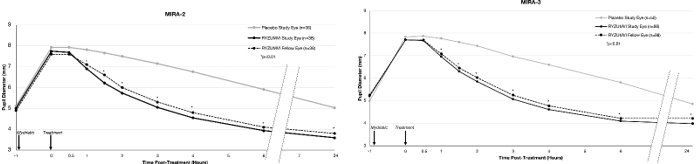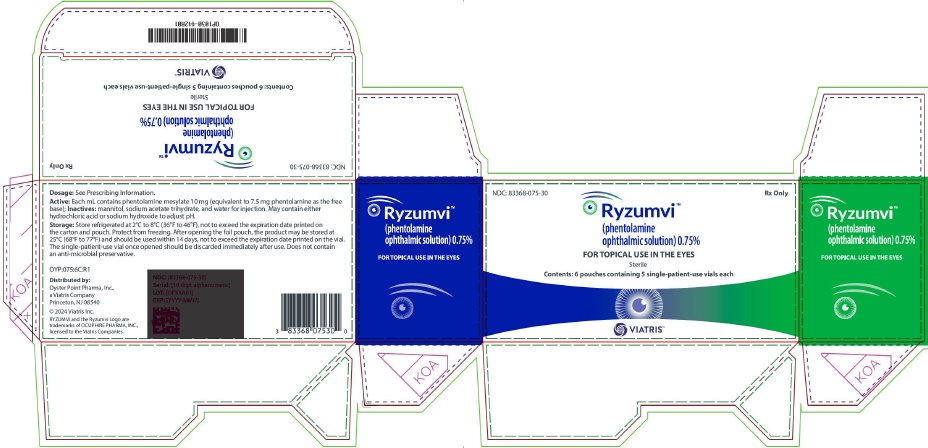 DRUG LABEL: Ryzumvi
NDC: 83368-075 | Form: SOLUTION/ DROPS
Manufacturer: Oyster Point Pharma, Inc.
Category: prescription | Type: HUMAN PRESCRIPTION DRUG LABEL
Date: 20240531

ACTIVE INGREDIENTS: PHENTOLAMINE MESYLATE 10 mg/1 mL
INACTIVE INGREDIENTS: MANNITOL; SODIUM ACETATE; WATER

HIGHLIGHTS OF PRESCRIBING INFORMATION

These highlights do not include all the information needed to use RYZUMVI safely and effectively. See full prescribing information for RYZUMVI.
RYZUMVI™ (phentolamine ophthalmic solution), for topical ophthalmic use
Initial U.S. Approval: 1952

1 INDICATIONS AND USAGE

Ryzumvi is an alpha adrenergic blocker indicated for the treatment of pharmacologically-induced mydriasis produced by adrenergic agonists (e.g., phenylephrine) or parasympatholytic (e.g., tropicamide) agents. (1)

2 DOSAGE AND ADMINISTRATION

- Adults and Pediatric Patients Aged 12 Years and Older: Instill 1 to 2 drops in each dilated eye following the completion of the ophthalmic examination or procedure to reverse mydriasis. (2)
- Pediatric Patients Aged 3 to 11 Years: Instill 1 drop in each dilated eye following the completion of the ophthalmic examination or procedure to reverse mydriasis. (2)

3 DOSAGE FORMS AND STRENGTHS

Ophthalmic solution: phentolamine 0.75% in a single-patient-use vial. (3)

4 CONTRAINDICATIONS

None. (4)

5 WARNINGS AND PRECAUTIONS

Uveitis: Ryzumvi is not recommended to be used in patients with active ocular inflammation. (5.1)

6 ADVERSE REACTIONS

The most common adverse reactions that have been reported are instillation site discomfort (16%), conjunctival hyperemia (12%), and dysgeusia (6%). (6.1)

To report SUSPECTED ADVERSE REACTIONS, contact Viatris at 1-877-446-3679 (1-877-4-INFO-RX) or FDA at 1-800-FDA-1088 or www.fda.gov/medwatch.

FULL PRESCRIBING INFORMATION

1 INDICATIONS AND USAGE

Ryzumvi is indicated for the treatment of pharmacologically-induced mydriasis produced by adrenergic agonists (e.g., phenylephrine) or parasympatholytic (e.g., tropicamide) agents.

2 DOSAGE AND ADMINISTRATION

Adults and Pediatric Patients Aged 12 Years or Older: Instill 1 or 2 drops in each dilated eye following the completion of the ophthalmic examination or procedure. If 2 drops are instilled, the second drop should be administered 5 minutes after the first drop.

Pediatric Patients Aged 3 to 11 Years: Instill 1 drop in each dilated eye following the completion of the ophthalmic examination or procedure.

One single-patient-use vial can be used to dose each dilated eye. Discard the single-patient-use vial immediately after use.

3 DOSAGE FORMS AND STRENGTHS

Ophthalmic solution: clear and colorless solution containing phentolamine 0.75% in a single-patient-use vial.

4 CONTRAINDICATIONS

None.

5 WARNINGS AND PRECAUTIONS

5.1 Uveitis

Ryzumvi is not recommended when active ocular inflammation (e.g., iritis) is present because adhesions (synechiae) may form between the iris and the lens.

5.2 Potential for Eye Injury or Contamination

To avoid the potential for eye injury or contamination, care should be taken to avoid touching the vial tip to the eye or to any other surface.

5.3 Use with Contact Lenses

Contact lens wearers should be advised to remove their lenses prior to the instillation of Ryzumvi and wait 10 minutes after dosing before reinserting their contact lenses.

6 ADVERSE REACTIONS

6.1 Clinical Trials Experience

Because clinical trials are conducted under widely varying conditions, adverse reaction rates observed in the clinical trials of a drug cannot be directly compared to rates in the clinical trials of another drug and may not reflect the rates observed in practice.

Ryzumvi was evaluated in 642 subjects in clinical trials across various subject populations. The most common ocular adverse reactions reported in > 5% of subjects were instillation site discomfort including pain, stinging, and burning (16%) and conjunctival hyperemia (12%). The only non-ocular adverse reaction reported in > 5% of subjects was dysgeusia (6%).

8 USE IN SPECIFIC POPULATIONS

8.1 Pregnancy

Risk Summary

There are no available data with Ryzumvi administration in pregnant women to inform a drug-associated risk. In animal toxicology studies, when phentolamine was administered orally to pregnant mice and rats during the period of organogenesis, skeletal immaturity and decreased growth was observed in the offspring at doses at least 24-times the recommended clinical dose. Additionally, a lower rate of implantation was seen in pregnant rats treated with phentolamine administered at least 60-times the recommended clinical dose. No malformations or embryofetal deaths were observed in the offspring of pregnant mice, rats, and rabbits administered phentolamine during the period of organogenesis at doses of at least 24-, 60-, and 20-times, respectively, the recommended clinical dose (see Data). Ryzumvi should only be used during pregnancy if the potential benefit justifies the potential risk to the fetus.

Data

Animal Data

Oral administration of phentolamine to pregnant rats and mice at doses at least 24-times the recommended clinical dose (based on a body weight per surface area (mg/m^2) comparison with a 60-kg human) resulted in slightly decreased growth and slight skeletal immaturity of the fetuses. Immaturity was manifested by increased incidence of incomplete or unossified calcanei and phalangeal nuclei of the hind limb and of incompletely ossified sternebrae. At oral phentolamine doses at least 60-times the recommended clinical dose (based on a mg/m^2 comparison with a 60-kg human), a slightly lower rate of implantation was found in rats. Phentolamine did not affect embryonic or fetal development in rabbits at oral doses at least 20-times the recommended dose (based on a mg/m^2 comparison with a 60-kg human). No malformations or embryofetal deaths were observed in the rat, mouse or rabbit studies.

8.2 Lactation

Risk Summary

There is no information regarding the presence of phentolamine in human milk, the effects on the breastfed infants, or the effects on milk production during lactation to inform risk of phentolamine ophthalmic solution 0.75% to an infant. The developmental and health benefits of breastfeeding should be considered along with the mother’s clinical need for Ryzumvi and any potential adverse effects on the breastfed child from Ryzumvi.

8.4 Pediatric Use

The safety and effectiveness of Ryzumvi have been established in pediatric patients aged 3 to 17 years. No overall differences have been observed between pediatric and adult subjects [see Clinical Studies (14)].

8.5 Geriatric Use

No overall differences in safety and effectiveness have been observed between elderly and younger adult subjects.

10 OVERDOSAGE

No deaths due to acute poisoning with phentolamine have been reported. Overdosage with parenterally administered phentolamine is characterized chiefly by cardiovascular disturbances, such as arrhythmias, tachycardia, hypotension, and possibly shock. In addition, the following might occur: excitation, headache, sweating, visual disturbances, nausea, vomiting, diarrhea, or hypoglycemia. There is no specific antidote; treatment consists of appropriate monitoring and supportive care. Substantial decreases in blood pressure or other evidence of shock-like conditions should be treated vigorously and promptly.

11 DESCRIPTION

Ryzumvi (phentolamine ophthalmic solution) 0.75% is a sterile, clear and colorless solution for topical ophthalmic use containing 1% phentolamine mesylate (equivalent to 0.75% phentolamine). The product does not contain an anti-microbial preservative. The chemical name of phentolamine mesylate is 3-[[(4,5-dihydro-1H-imidazol-2-yl)methyl](4-methylphenyl)amino]phenol; methanesulfonic acid (parent phentolamine: [3-[[(4,5-dihydro-1H-imidazol-2-yl)methyl](4-methylphenyl)amino]phenol]) and the molecular formula is C18H23N3O4S (parent C17H19N3O). The molecular weight of phentolamine mesylate is 377.46 and the chemical structure is:

Each mL of Ryzumvi contains phentolamine mesylate 10 mg as the active ingredient (equivalent to 7.5 mg phentolamine as the free base). Inactive ingredients are mannitol, sodium acetate trihydrate, and water for injection. Hydrochloric acid and/or sodium hydroxide are added to adjust pH (4.5 to 5.5), and the solution is overlaid with nitrogen.

12 CLINICAL PHARMACOLOGY

12.1 Mechanism of Action

Ryzumvi is a relatively non-selective alpha-1 and alpha-2 adrenergic antagonist. Dilation of the pupil is primarily controlled by the radial iris dilator muscles surrounding the pupil; these muscles are activated by the alpha-1 adrenergic receptors. Phentolamine reversibly binds to these receptors on the iris dilator muscle, thereby reducing pupil diameter. Phentolamine directly antagonizes the mydriatic effect of an α-1 adrenergic agonist, and indirectly reverses mydriasis induced by muscarinic antagonist effects on the iris sphincter muscle.

12.2 Pharmacodynamics

The onset of action after administration of Ryzumvi generally occurs in 30 minutes, with the maximal effect seen in 60 to 90 minutes, and the effect lasting at least 24 hours.

12.3 Pharmacokinetics

Phentolamine systemic exposure was evaluated in a Phase 3 trial (MIRA-3) following topical ocular administration of a total of 3 drops, each of 0.03 mL, of phentolamine ophthalmic solution 0.75%. The peak concentration levels are achieved between 15 minutes and 1 hour after dosing with the median value of 0.45 ng/mL.

13 NONCLINICAL TOXICOLOGY

13.1 Carcinogenesis, Mutagenesis, Impairment of Fertility

Carcinogenesis

Carcinogenicity studies with Ryzumvi have not been conducted.

Mutagenesis

Phentolamine was not mutagenic in the in vitro bacterial reverse mutation (Ames) assay. In the in vitro chromosomal aberration study in Chinese hamster ovary cells, numerical aberrations were slightly increased after a 4-hour exposure to phentolamine without metabolic activation, and structural aberrations were slightly increased after a 4-hour exposure to phentolamine with metabolic activation only at the highest concentrations tested, but neither numerical nor structural aberrations were increased after a 20-hour exposure without metabolic activation. Phentolamine was not clastogenic in two in vivo mouse micronucleus assays.

Impairment of Fertility

The effect of phentolamine on female fertility has not been studied. Male rats treated with oral phentolamine for 9 weeks (4 weeks prior to mating, 3 weeks during the mating period and 2 weeks after mating) were mated with untreated females. At doses up to 648-times human therapeutic exposure levels at the Cmax, no adverse effects on male fertility parameters or on reproductive parameters in the untreated females mated with the treated males were observed.

14 CLINICAL STUDIES

The efficacy of Ryzumvi for the reversal of mydriasis was demonstrated in two, randomized, double-masked, vehicle-controlled trials; MIRA-2 (NCT#04620213) and MIRA-3 (NCT#05134974). A total of 553 subjects, aged 12 to 80 years, who had mydriasis induced by instillation of phenylephrine or tropicamide or a combination of hydroxyamphetamine hydrobromide and tropicamide (Paremyd®) were randomized. Subjects with light and dark irides were included in both trials. Two drops (study eye) or one drop (fellow eye) of Ryzumvi or placebo (vehicle) were administered one hour after instillation of the mydriatic agent. The percentage of subjects with study eyes returning to ≤ 0.2 mm from baseline pupil diameter was statistically significantly greater (p < 0.01) at all time points measured from 60 minutes through 24 hours in the Ryzumvi group compared with the placebo (vehicle) group across both of the MIRA-2 and MIRA-3 trials (see Figure 1).

Figure 1. Percentage of Subjects with Study Eyes Returning to ≤ 0.2 mm from Baseline Pupil Diameter by Time Point in the MIRA-2 and MIRA-3 Trials

The efficacy of MIRA-2 and MIRA-3 also showed that the change from maximum pupil dilation in study eyes and fellow eyes was statistically significantly different between the Ryzumvi-treated group and the placebo-treated group at all time points from 60 minutes through 24 hours post-treatment (p < 0.01). Pupil size at 24 hours was 1 mm smaller than baseline. These results were consistent regardless of whether phenylephrine or tropicamide/Paremyd were used as mydriatic agents (Figure 2, Figure 3; respectively).

Figure 2: Pupil Dilation by Time Point with Phenylephrine as Mydriatic Agent in MIRA-2 and MIRA-3 Trials (mITT Population)
Figure 3: Pupil Dilation by Time Point with Tropicamide or Paremyd as Mydriatic Agent in MIRA-2 and MIRA-3 Trials (mITT Population)

The efficacy of Ryzumvi was similar for all age ranges including pediatric subjects aged 3 to 17 years. Pediatric subjects aged 12 to 17 years (n = 27) were treated in MIRA-2 and MIRA-3 and pediatric subjects, aged 3 to 11 years (n = 11) were treated in MIRA-4, (NCT#05223478).

16 HOW SUPPLIED/STORAGE AND HANDLING

Ryzumvi (phentolamine ophthalmic solution) 0.75% is supplied as a sterile, clear, and colorless solution for topical ophthalmic use contained in a translucent, low-density polyethylene, single-patient-use vial with a 0.31 mL fill. One strip of 5 single-patient-use vials is packaged into a foil pouch, with 6 foil pouches in a carton. One single-patient-use vial should be dispensed for each patient, and it can be used to dose both eyes.

Carton of 30 single-patient-use vials – NDC-83368-075-30

Storage and Handling:

Store refrigerated at 2°C to 8°C (36°F to 46°F), not to exceed the expiration date printed on the carton and pouch. Protect from freezing.

After opening the foil pouch, the product may be stored at 25ºC (68°F to 77ºF) and should be used within 14 days, not to exceed the expiration date printed on the vial. The single-patient-use vial once opened should be discarded immediately after use.

© 2024 Viatris Inc.

RYZUMVI is a trademark of OCUPHIRE PHARMA, INC., licensed to the Viatris Companies.

The brands listed are trademarks of their respective owners.

Distributed by:
Oyster Point Pharma, Inc., a Viatris Company
Princeton, NJ 08540

OYP:RZVMI:R1

PRINCIPAL DISPLAY PANEL – 0.75%

NDC: 83368-075-30 Rx Only

Ryzumvi™
(phentolamine
ophthalmic solution) 0.75%

FOR TOPICAL USE IN THE EYES

Sterile

Contents: 6 pouches containing 5 single-patient-use vials each

Dosage: See Prescribing Information.

Active: Each mL contains phentolamine mesylate 10 mg (equivalent to 7.5 mg phentolamine as the free
base); Inactives: mannitol, sodium acetate trihydrate, and water for injection. May contain either
hydrochloric acid or sodium hydroxide to adjust pH.

Storage: Store refrigerated at 2°c to 8°C (36°F to 46°F), not to exceed the expiration date printed on
the carton and pouch. Protect from freezing. After opening the foil pouch, the product may be stored at
25°C (68°F to 77°F) and should be used within 14 days, not to exceed the expiration date printed on the vial.

The single-patient-use vial once opened should be discarded immediately after use. Does not contain
an anti-microbial preservative.

OYP:075:6C:R1

Distributed by:
Oyster Point Pharma, Inc.,
a Viatris company
Princeton, NJ 08540

© 2024 Viatris Inc.

RYZUMVI and the Ryzumvi Logo are
trademarks of OCUPHIRE PHARMA, INC.,
licensed to the Viatris Companies.